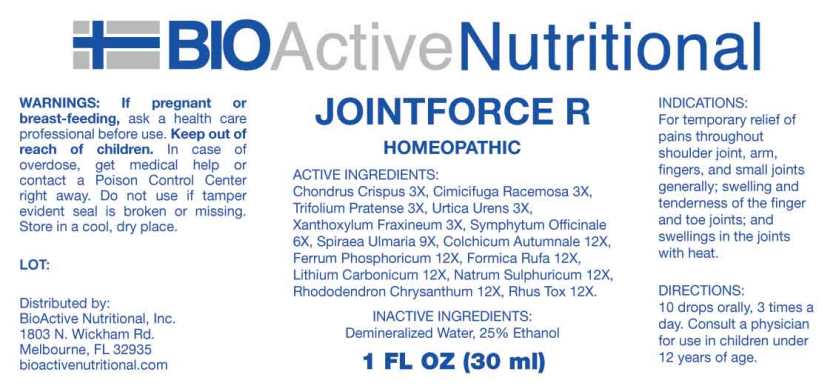 DRUG LABEL: Jointforce R
NDC: 43857-0602 | Form: LIQUID
Manufacturer: BioActive Nutritional, Inc.
Category: homeopathic | Type: HUMAN OTC DRUG LABEL
Date: 20230607

ACTIVE INGREDIENTS: CHONDRUS CRISPUS 3 [hp_X]/1 mL; BLACK COHOSH 3 [hp_X]/1 mL; TRIFOLIUM PRATENSE FLOWER 3 [hp_X]/1 mL; URTICA URENS WHOLE 3 [hp_X]/1 mL; ZANTHOXYLUM AMERICANUM BARK 3 [hp_X]/1 mL; COMFREY ROOT 6 [hp_X]/1 mL; FILIPENDULA ULMARIA ROOT 9 [hp_X]/1 mL; COLCHICUM AUTUMNALE BULB 12 [hp_X]/1 mL; FERROSOFERRIC PHOSPHATE 12 [hp_X]/1 mL; FORMICA RUFA 12 [hp_X]/1 mL; LITHIUM CARBONATE 12 [hp_X]/1 mL; SODIUM SULFATE 12 [hp_X]/1 mL; RHODODENDRON AUREUM LEAF 12 [hp_X]/1 mL; TOXICODENDRON PUBESCENS LEAF 12 [hp_X]/1 mL
INACTIVE INGREDIENTS: WATER; ALCOHOL

Drug Facts:

INACTIVE INGREDIENTS:

Chondrus Crispus 3X, Cimicifuga Racemosa 3X, Trifolium Pratense 3X, Urtica Urens 3X, Xanthoxylum Fraxineum 3X, Symphytum Officinale 6X, Spiraea Ulmaria 9X, Colchicum Autumnale 12X, Ferrum Phosphoricum 12X, Formica Rufa 12X, Lithium Carbonicum 12X, Natrum Sulphuricum 12X, Rhododendron Chrysanthum 12X, Rhus Toxicodendron 12X.

INDICATIONS:

For temporary relief of pains throughout shoulder joint, arm, fingers, and small joints generally; swelling and tenderness of the finger and toe joints; and swellings in the joints with heat.

WARNINGS:

If pregnant or breast-feeding, ask a health care professional before use.

Keep out of reach of children. In case of overdose, get medical help or contact a Poison Control Center right away.

Do not use if tamper evident seal is broken or missing.

Store in cool, dry place.

Keep out of reach of children. In case of overdose, get medical help or contact a Poison Control Center right away.

DIRECTIONS:

10 drops orally, 3 times a day. Consult a physician for use in children under 12 years of age.

INDICATIONS:

For temporary relief of pains throughout shoulder joint, arm, fingers, and small joints generally; swelling and tenderness of the finger and toe joints; and swellings in the joints with heat.

INACTIVE INGREDIENTS:

Demineralized Water, 25% Ethanol

QUESTIONS:

Distributed by:

BioActive Nutritional, Inc.

1803 N. Wickham Rd.

Melbourne, FL 32935

bioactivenutritional.com

PACKAGE LABEL DISPLAY:

BIOActive Nutritional

JOINTFORCE R

HOMEOPATHIC

1 FL OZ (30 ml)